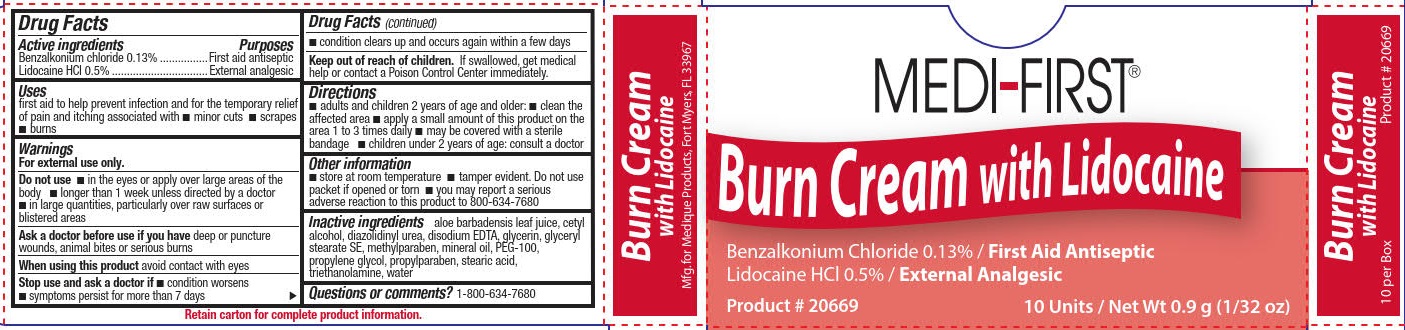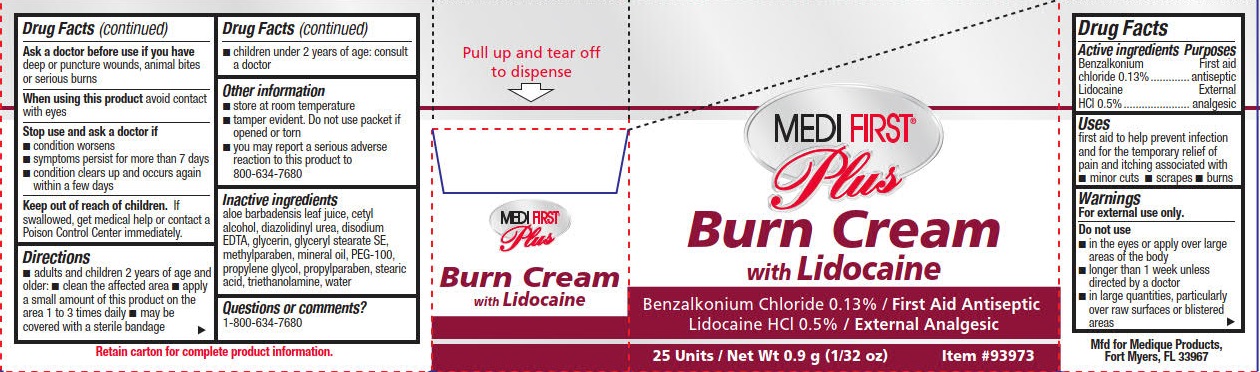 DRUG LABEL: Medi-First Plus Burn with Lidocaine
NDC: 47682-930 | Form: CREAM
Manufacturer: Unifirst First Aid Corporation
Category: otc | Type: HUMAN OTC DRUG LABEL
Date: 20240117

ACTIVE INGREDIENTS: BENZALKONIUM CHLORIDE 1.3 mg/1 g; LIDOCAINE HYDROCHLORIDE 5 mg/1 g
INACTIVE INGREDIENTS: TROLAMINE; GLYCERIN; WATER; EDETATE DISODIUM; METHYLPARABEN; GLYCERYL STEARATE SE; PROPYLPARABEN; CETYL ALCOHOL; DIAZOLIDINYL UREA; PROPYLENE GLYCOL; GLYCERYL STEARATE/PEG-100 STEARATE; STEARIC ACID; MINERAL OIL; ALOE VERA LEAF

Medi-First Burn Cream with Lidocaine

Drug Facts

Active ingredients

Benzalkonium chloride 0.13%

Lidocaine HCl 0.5%

Purposes

First aid antiseptic

External analgesic

Uses

first aid to help prevent infection and for the temporary relief of pain and itching associated with

- minor cuts
- scrapes
- burns

Warnings

For external use only.

Do not use

- in the eyes or apply over large areas of the body
- longer than 1 week unless directed by a doctor
- in large quantities, particularly over raw surfaces or blistered areas

Ask a doctor before use if you have

deep or puncture wounds, animal bites or serious burns

When using this product avoid contact with the eyes

Stop use and ask a doctor if

- condition worsens
- symptoms persist for more than 7 days
- condition clears up and occurs again within a few days

Keep out of reach of children. If swallowed, get medical help or contact a Poison Control Center immediately.

Directions

- adults and children 2 years of age and older:
  - clean the affected area
  - apply a small amount of this product on the area 1 to 3 times daily
  - may be covered with a sterile bandage

- children under 2 years of age: consult a doctor

Other information

- store at room temperature
- tamper evident. Do not use if packet is opened or torn
- you may report a serious adverse reaction to this product to 800-634-7680

Inactive ingredients

aloe barbadensis leaf juice, cetyl alcohol, diazolidinyl urea, disodiun EDTA,, glycerin, glyceryl stearate SE, methylparaben, mineral oil, PEG 100, propylene glycol, propylparaben, stearic acid, triethanolamine, water

Questions or comments? 1-800-634-7680

PACKAGE LABEL

Medi-First®

Burn Cream with Lidocaine

Benzalkonium Chloride 0.13% / First Aid Antiseptic

Lidocaine HCl 0.5% / External Analgesic

Product # 20669

10 Units Net Wt 0.9 g (1/32 oz)

PACKAGE LABEL

Medi-First® Plus

Burn Cream with Lidocaine

Benzalkonium Chloride 0.13% / First Aid Antiseptic

Lidocaine HCl 0.5% / External Analgesic

25 Units of 0.9 g Packets

Item #93973